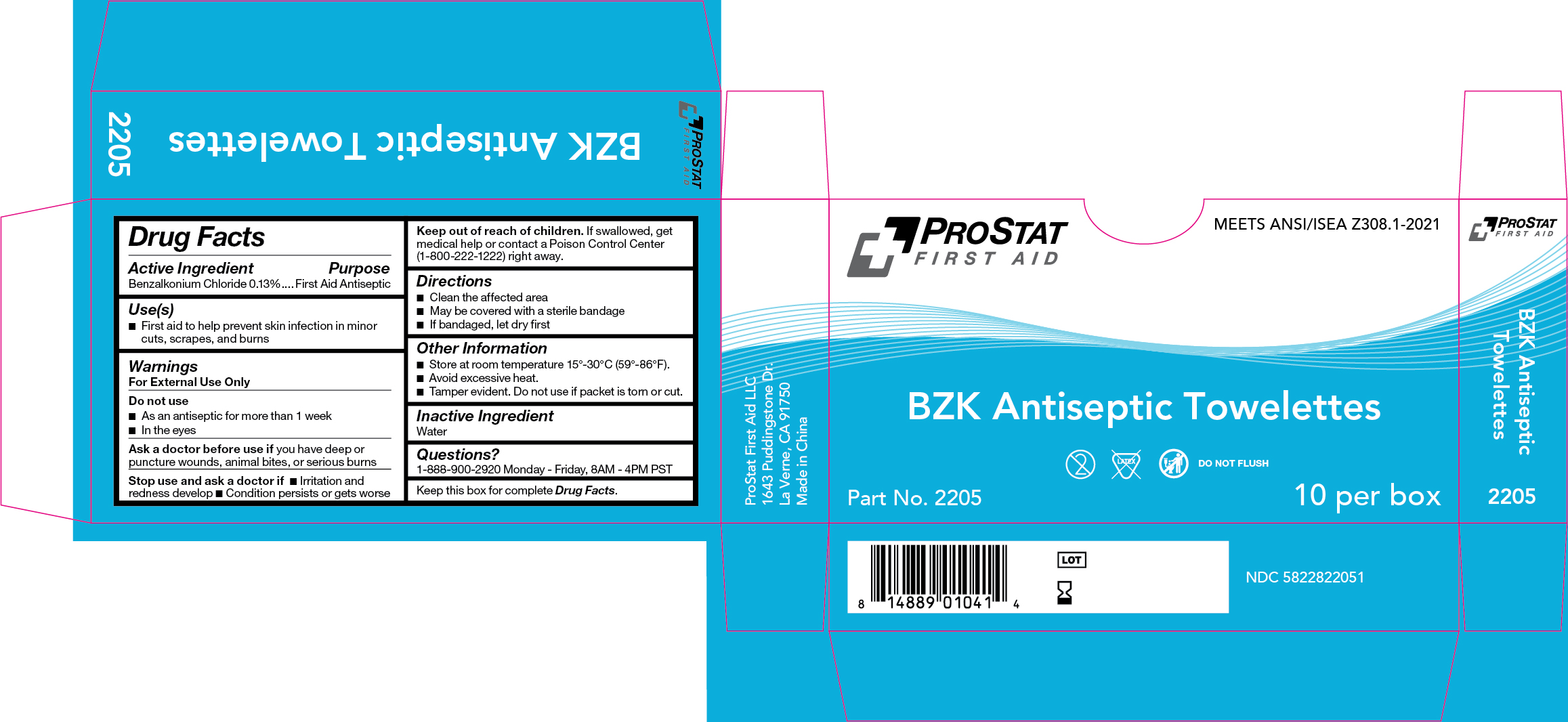 DRUG LABEL: PS-2205 BZK Antiseptic Towelettes
NDC: 58228-2205 | Form: SWAB
Manufacturer: ProStat First Aid LLC
Category: otc | Type: HUMAN OTC DRUG LABEL
Date: 20251215

ACTIVE INGREDIENTS: BENZALKONIUM CHLORIDE 1.3 mg/1 mL
INACTIVE INGREDIENTS: WATER

PS-2205 BZK Antiseptic Towelettes

Active Ingredient

Benzalkonium Chloride 0.13%

Purpose

First Aid Antiseptic

Use(s)

First aid to help prevent skin infection in minor cuts, scrapes, and burns

Warnings

For External Use Only

Do not use

• As an antiseptic for more than 1 week

• In the eyes

Ask a doctor before use if

You have deep or puncture wounds, animal bites, or serious burns

Stop use and ask a doctor if

• Irritation and redness develop • Condition persists or gets worse

Keep out of reach of children.

If swallowed, get medical help or contact a Poison Control Center (1-800-222-1222) right away.

Directions

• Clean the affected area

• May be covered with a sterile bandage

• If bandaged, let dry first

Other Information

• Store at room temperature 15º-30ºC (59º-86ºF).

• Avoid excessive heat.

• Tamper evident. Do not use if packet is torn or cut.

Inactive Ingredient

Water

Questions?

1-888-900-2920 Monday - Friday, 8AM - 4PM PST

Label

PS-2205 BZK Antiseptic Toweletts